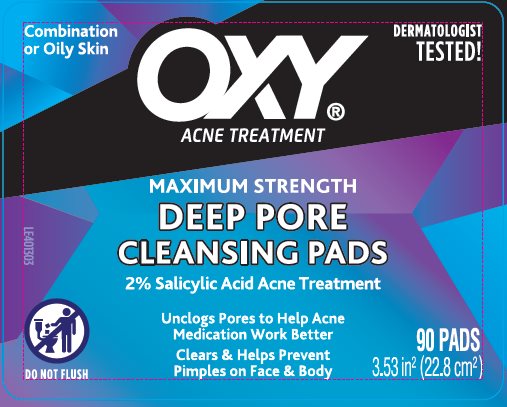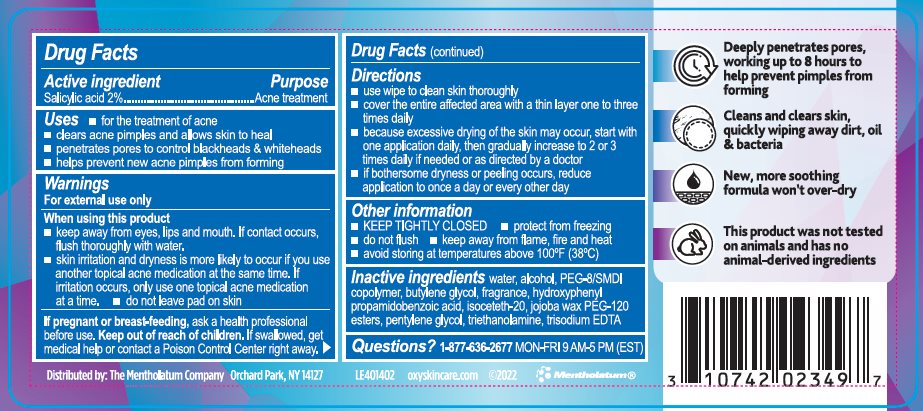 DRUG LABEL: OXY Deep Pore Cleansing Pads
NDC: 10742-4204 | Form: SWAB
Manufacturer: The Mentholatum Company
Category: otc | Type: HUMAN OTC DRUG LABEL
Date: 20251029

ACTIVE INGREDIENTS: SALICYLIC ACID 20 mg/1 1
INACTIVE INGREDIENTS: ALCOHOL; WATER; PEG-8/SMDI COPOLYMER; BUTYLENE GLYCOL; HYDROXYPHENYL PROPAMIDOBENZOIC ACID; ISOCETETH-20; SIMMONDSIA CHINENSIS SEED WAX; PENTYLENE GLYCOL; TROLAMINE; EDETATE TRISODIUM

Drug Facts - OXY Deep Pore Cleansing Pads

Active ingredient

Salicylic acid 2%

Purpose

Salicylic acid - Acne treatment

Uses

- for the treatment of acne
- clears acne pimples and allows skin to heal
- penetrates pores to control blackheads & whiteheads
- helps prevent new acne pimples from forming

Warnings

For external use only

When using this product

- keep away from eyes, lips and mouth. If contact occurs, flush thoroughly with water.
- skin irritation and dryness is more likely to occur if you use another topical acne medication at the same time. If irritation occurs, only use one topical acne medication at a time.
- do not leave pad on skin

If pregnant or breast-feeding

ask a health professional before use.

Keep out of reach of children.

If swallowed, get medical help or contact a Poison Control Center right away.

Directions

- use wipe to clean skin thoroughly
- cover the entire affected area with a thin layer one to three times daily
- because excessive drying of the skin may occur, start with one application daily, then gradually increase to 2 or 3 times daily if needed or as directed by a doctor
- if bothersome dryness or peeling occurs, reduce application to once a day or every other day

Other information

- KEEP TIGHTLY CLOSED
- protect from freezing
- do not flush
- keep away from flame, fire and heat
- avoid storing at temperatures above 100˚F (38˚C)

Inactive ingredients

water, alcohol, PEG-8/SMDI copolymer, butylene glycol, fragrance, hydroxyphenyl propamidobenzoic acid, isoceteth-20, jojoba wax PEG-120 esters, pentylene glycol, triethanolamine, trisodium EDTA

Questions?

1-877-636-2677 MON-FRI 9 AM - 5 PM (EST)